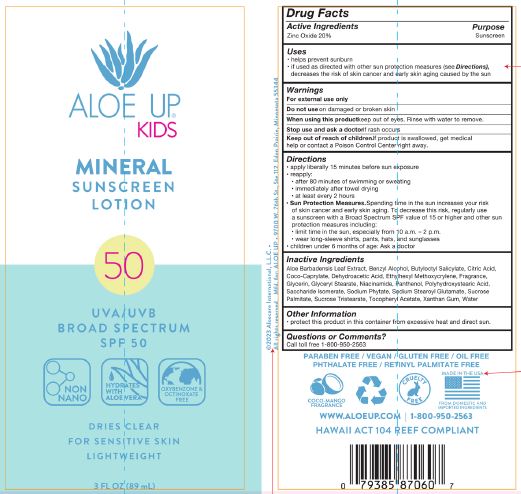 DRUG LABEL: Aloe Up SPF 50 Kids Mineral
NDC: 61477-236 | Form: LOTION
Manufacturer: Aloe International, LLC
Category: otc | Type: HUMAN OTC DRUG LABEL
Date: 20250618

ACTIVE INGREDIENTS: ZINC OXIDE 20 g/100 g
INACTIVE INGREDIENTS: SUCROSE TRISTEARATE; .ALPHA.-TOCOPHEROL ACETATE; FRAGRANCE 13576; GLYCERIN; GLYCERYL STEARATE; PANTHENOL; SACCHARIDE ISOMERATE; SODIUM PHYTATE; ALOE VERA LEAF; BENZYL ALCOHOL; DEHYDROACETIC ACID; ETHYLHEXYL METHOXYCRYLENE; POLYHYDROXYSTEARIC ACID (2300 MW); SODIUM STEAROYL GLUTAMATE; SUCROSE PALMITATE; WATER; XANTHAN GUM; NIACINAMIDE; COCO-CAPRYLATE; BUTYLOCTYL SALICYLATE; CITRIC ACID

Aloe Up SPF 50 Kids Mineral Sunscreen Lotion 3 fl.oz

ACTIVE INGREDIENT

Zinc Oxide 20%

PURPOSE

Sunscreen

INDICATIONS AND USAGE

- helps prevent sunburn
- if used as directed with other sun protection measures (see Directions), decreases the risk of skin cancer and early skin aging caused by the sun

WARNINGS

For external use only

Do not use on damaged or broken skin

When using this product keep out of eyes. Rinse with water to remove.

Stop use and ask a doctor if rash occurs

Keep out of reach of children. If product is swallowed, get medical help or contact a Poison Control Center right away.

DOSAGE AND ADMINISTRATION

- apply liberally 15 minutes before sun exposure
- reapply:
- after 80 minutes of swimming or sweating
- immediately after towel drying
- at least every 2 hours
- Sun Protection Measures.Spendind time in the sun icnreases your risk of skin cancer and early skin aging. To decrease this risk, regularly use a sunscreen with a Broad Spectrum SPF value of 15 or higher and other sun protection measures including:
- limite time in the sun, especially from 10am - 2pm
- wear long-sleeve shirts, pants, hats, and sunglasses
- children under 6 months of age: Ask a doctor

OTHER SAFETY INFORMATION

protect this product in this container from excessive heat and direct sun.

INACTIVE INGREDIENT

Aloe Barbadensis Leaf Extract

Benzyl Alcohol

Butyloctyl Salicylate

Citric Acid

Coco-Caprylate

Dehydroacetic Acid

Ethylhexyl Methoxycrylene

Fragrance

Glycerin

Glyceryl Stearate

Niacinamide

Panthenol

Polyhydroxystearic Acid

Saccharide Isomerate

Sodium Phytate

Sodium Stearoyl Glutamate

Sucrose Palmitate

Sucrose Tristearate

Tocopheryl Acetate

Water

Xathan Gum

Questions or Comments?

Call toll free 1-800-950-2563